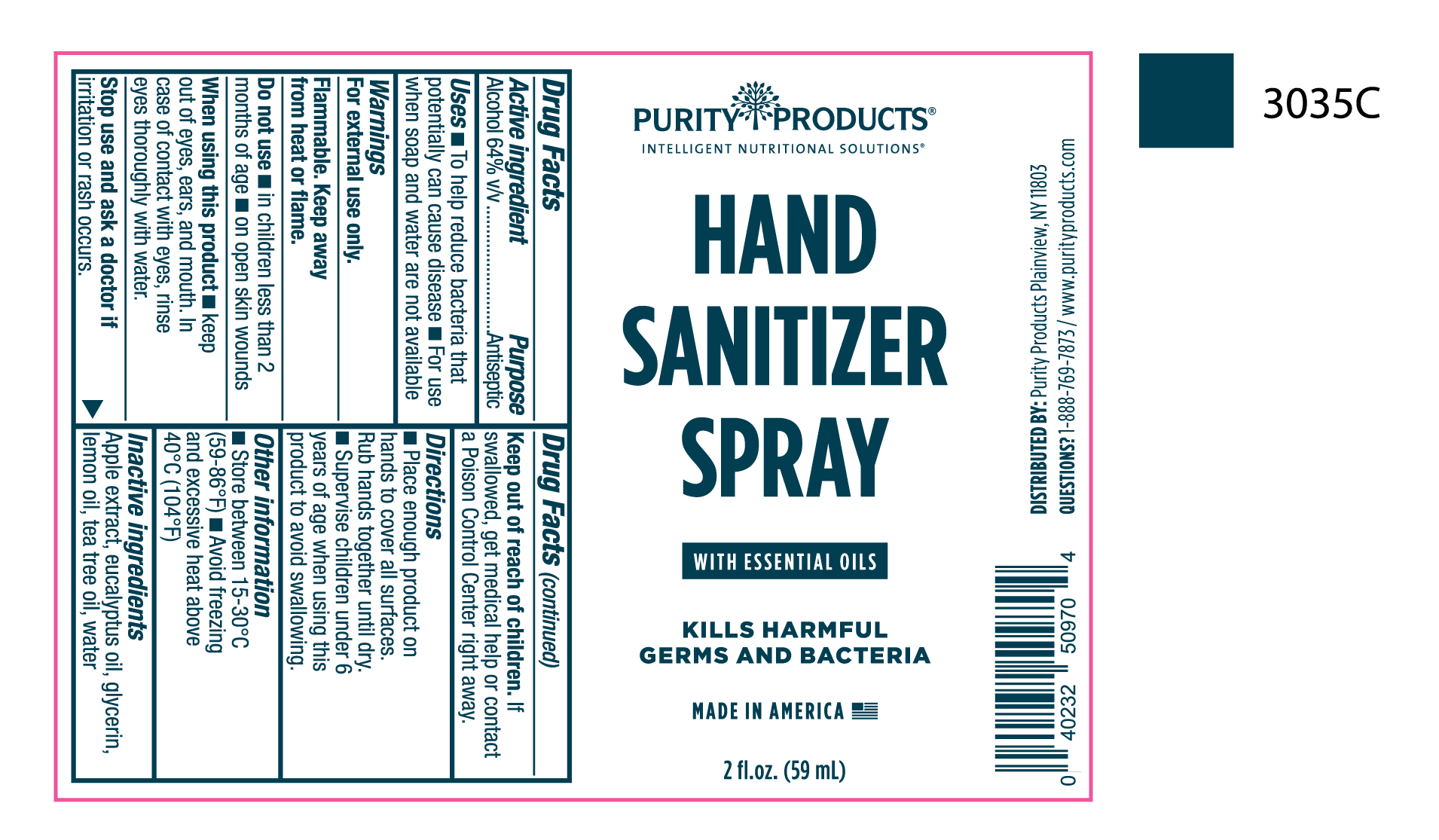 DRUG LABEL: Hand Sanitizer
NDC: 71003-005 | Form: SPRAY
Manufacturer: Water Pure, Inc. d.b.a. Purity Products, Inc.
Category: otc | Type: HUMAN OTC DRUG LABEL
Date: 20220120

ACTIVE INGREDIENTS: ALCOHOL 64.4 mL/100 mL
INACTIVE INGREDIENTS: LEMON OIL 0.06 mL/100 mL; GLYCERIN 1.75 mL/100 mL; APPLE FRUIT OIL 1.75 mL/100 mL; WATER 32 mL/100 mL; TEA TREE OIL 0.02 mL/100 mL; EUCALYPTUS OIL 0.02 mL/100 mL

Active Ingredient(s)

Alcohol 64% v/v. Purpose: Antiseptic

Purpose

Antiseptic, Hand Sanitizer

Use

Hand Sanitizer to help reduce bacteria that potentially can cause disease. For use when soap and water are not available.

Warnings

For external use only. Flammable. Keep away from heat or flame

Do not use

- in children less than 2 months of age
- on open skin wounds

When using this product keep out of eyes, ears, and mouth. In case of contact with eyes, rinse eyes thoroughly with water.
Stop use and ask a doctor if irritation or rash occurs. These may be signs of a serious condition.
Keep out of reach of children. If swallowed, get medical help or contact a Poison Control Center right away.

Stop use and ask a doctor if irritation or rash occurs. These may be signs of a serious condition.

Keep out of reach of children. If swallowed, get medical help or contact a Poison Control Center right away.

Directions

- Place enough product on hands to cover all surfaces. Rub hands together until dry.
- Supervise children under 6 years of age when using this product to avoid swallowing.

Other information

- Store between 15-30C (59-86F)
- Avoid freezing and excessive heat above 40C (104F)

Inactive ingredients

apple extract, eucalyptus oil, glycerin, lemon oil, tea tree oil, water

Package Label - Principal Display Panel

60 mL NDC: 71003-005-00